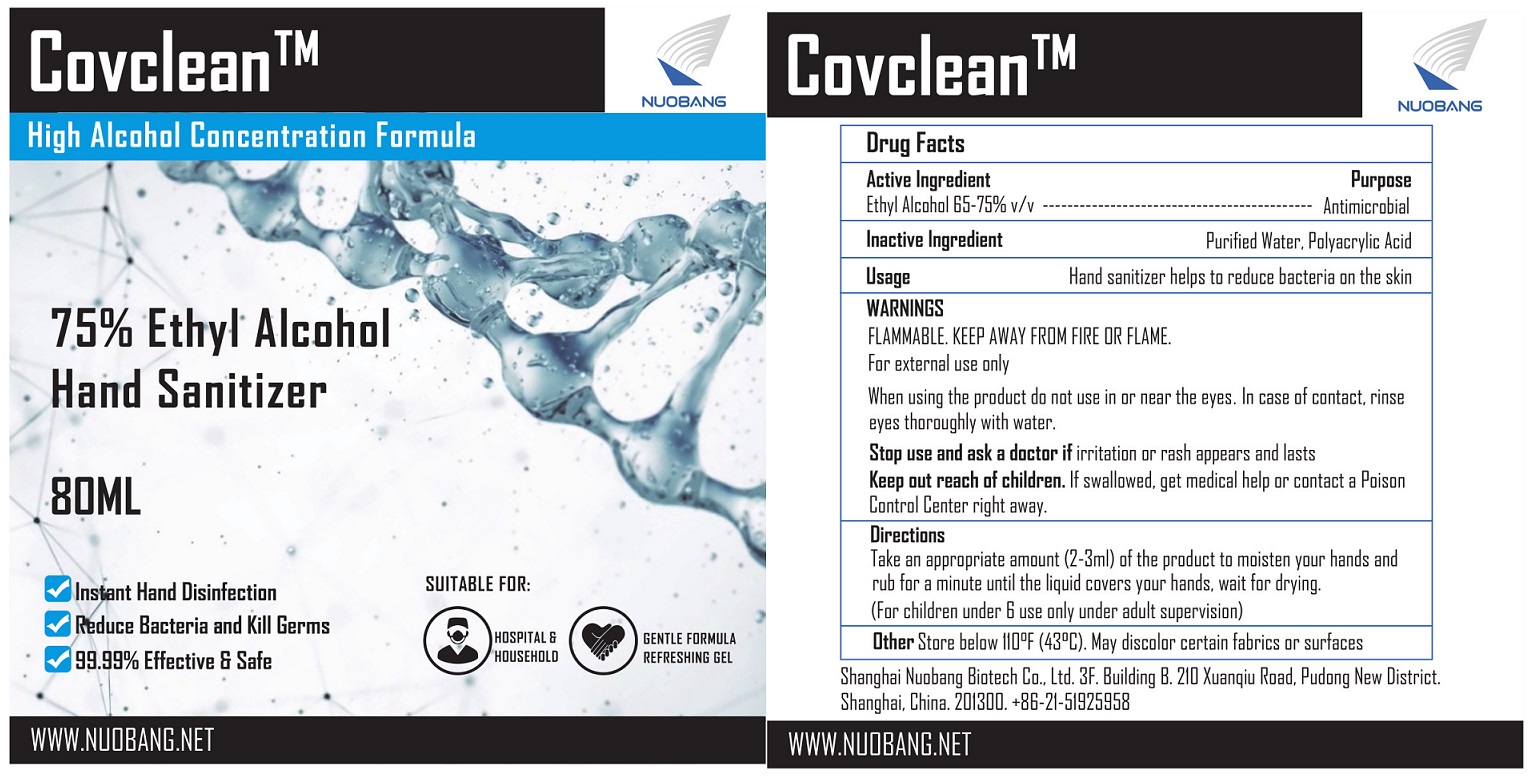 DRUG LABEL: Covclean 75% Ethyl Alcohol Hand Sanitizer
NDC: 75313-1012 | Form: GEL
Manufacturer: Shanghai Nuobang Biotech Co., Ltd.
Category: otc | Type: HUMAN OTC DRUG LABEL
Date: 20200427

ACTIVE INGREDIENTS: ALCOHOL 60 mL/80 mL
INACTIVE INGREDIENTS: TROLAMINE; WATER; HYALURONATE SODIUM; CARBOMER HOMOPOLYMER, UNSPECIFIED TYPE

NuoBang, Hand Sanitizer, 75% Alcohol, Liquid, 80mL

Active Ingredient(s)

Enthyl alcohol 75% v/v. Purpose: Antimicrobial

Purpose

Antimicrobial

Use

Hand sanitizer to help reduce bacteria on the skin.

Recommended for repeated use.

Warnings

Flammable.

Keep away from heat or flame.

For external use only.

Do not use if allergic to ethanol.

When using this product do not use in or near the eyes.

In case of contact, rinse eyes thoroughly with water.

Stop use and ask a doctor if irritation or rash appears or lasts.

Keep out of reach of children. If swallowed, get medical help or contact a Poison Control Center right away.

Directions

Take an appropriate amount (2-3ml) of the product to moisten your hands and rub for a minute until the liquid covers your hands, wait for drying.

(For children under 6 use only under adult supervision)

Other information

Store below 110℉ (43℃).

May discolor certain fabrics or surfaces.

Inactive ingredients

Purified water (aqua), Triethanolamine, Carbomer, Sodium hyaluronate.